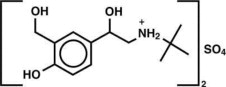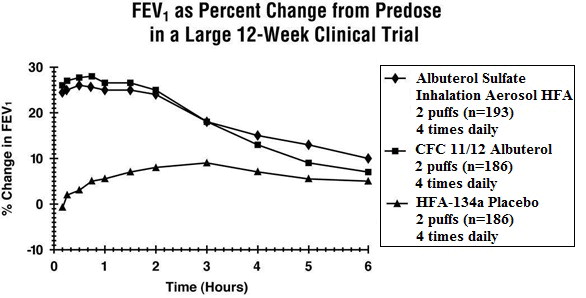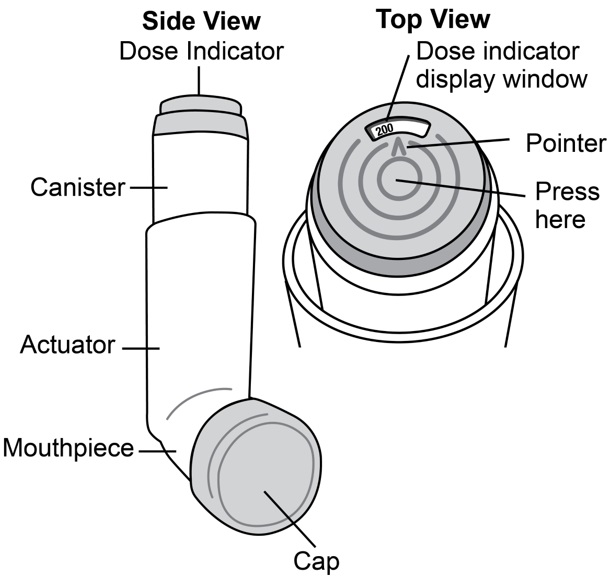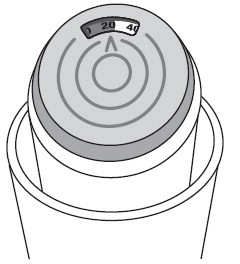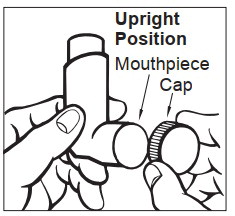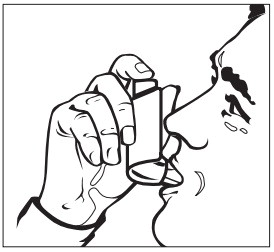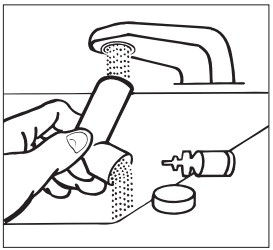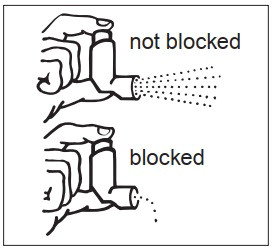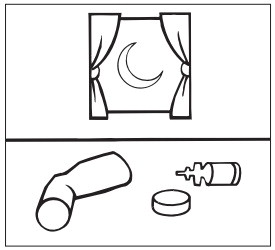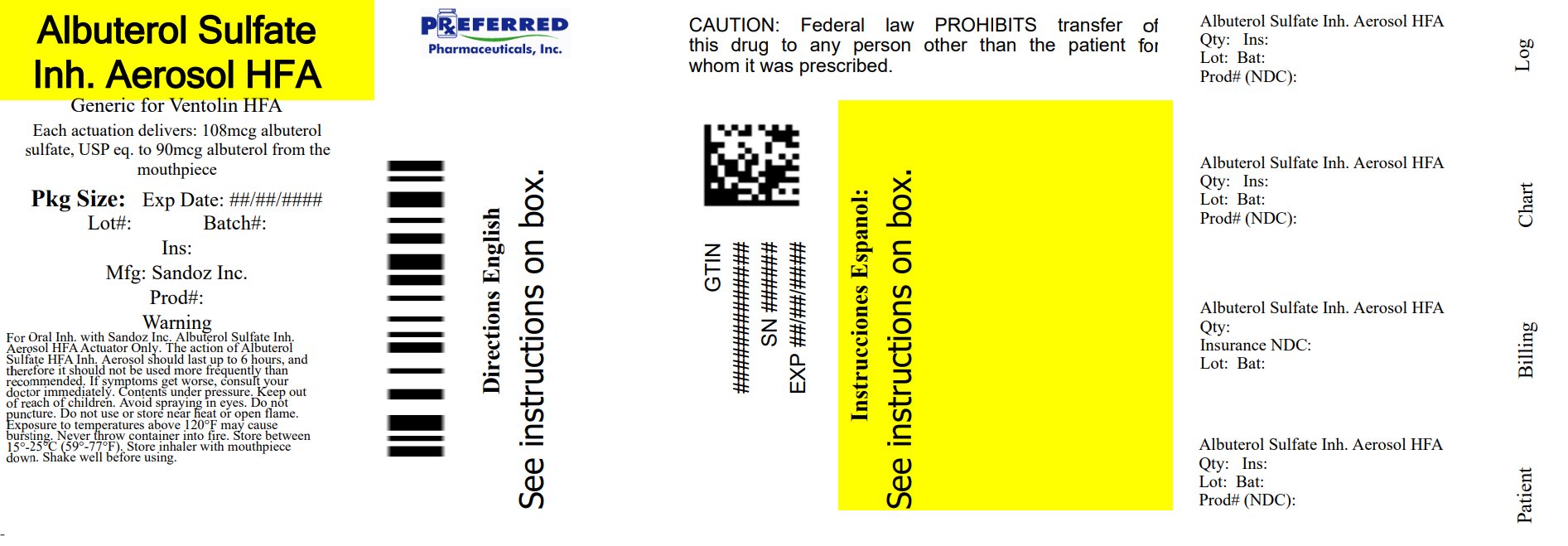 DRUG LABEL: Albuterol Sulfate
NDC: 68788-7996 | Form: AEROSOL, METERED
Manufacturer: Preferred Pharmaceuticals Inc.
Category: prescription | Type: HUMAN PRESCRIPTION DRUG LABEL
Date: 20260114

ACTIVE INGREDIENTS: ALBUTEROL SULFATE 108 ug/1 1
INACTIVE INGREDIENTS: ALCOHOL; NORFLURANE; OLEIC ACID

Albuterol Sulfate Inhalation Aerosol with Dose Indicator

FOR ORAL INHALATION ONLY

Prescribing Information

DESCRIPTION

The active component of Albuterol Sulfate Inhalation Aerosol is albuterol sulfate, USP racemic α ^1 [(tert-Butylamino)methyl]-4-hydroxy- m-xylene-α,α'-diol sulfate (2:1)(salt), a relatively selective beta 2-adrenergic bronchodilator having the following chemical structure:

Albuterol sulfate is the official generic name in the United States. The World Health Organization recommended name for the drug is salbutamol sulfate. The molecular weight of albuterol sulfate is 576.7, and the empirical formula is (C 13H 21NO 3) 2•H 2SO 4. Albuterol sulfate is a white to off-white crystalline solid. It is soluble in water and slightly soluble in ethanol. Albuterol Sulfate Inhalation Aerosol is a pressurized metered-dose aerosol unit for oral inhalation. It contains a microcrystalline suspension of albuterol sulfate in propellant HFA-134a (1,1,1,2-tetrafluoroethane), ethanol, and oleic acid.

Each actuation delivers 120 mcg albuterol sulfate, USP from the valve and 108 mcg albuterol sulfate, USP from the mouthpiece (equivalent to 90 mcg of albuterol base from the mouthpiece). Each canister provides 200 inhalations. It is recommended to prime the inhaler before using for the first time and in cases where the inhaler has not been used for more than 2 weeks by releasing four “test sprays” into the air, away from the face.

This product does not contain chlorofluorocarbons (CFCs) as the propellant.

CLINICAL PHARMACOLOGY

Mechanism of Action In vitro studies and in vivo pharmacologic studies have demonstrated that albuterol has a preferential effect on beta 2-adrenergic receptors compared with isoproterenol. While it is recognized that beta 2-adrenergic receptors are the predominant receptors on bronchial smooth muscle, data indicate that there is a population of beta 2-receptors in the human heart existing in a concentration between 10% and 50% of cardiac beta-adrenergic receptors. The precise function of these receptors has not been established. (See WARNINGS, Cardiovascular Effects section.)

Activation of beta 2-adrenergic receptors on airway smooth muscle leads to the activation of adenylcyclase and to an increase in the intracellular concentration of cyclic-3',5'-adenosine monophosphate (cyclic AMP). This increase of cyclic AMP leads to the activation of protein kinase A, which inhibits the phosphorylation of myosin and lowers intracellular ionic calcium concentrations, resulting in relaxation. Albuterol relaxes the smooth muscles of all airways, from the trachea to the terminal bronchioles. Albuterol acts as a functional antagonist to relax the airway irrespective of the spasmogen involved, thus protecting against all bronchoconstrictor challenges. Increased cyclic AMP concentrations are also associated with the inhibition of release of mediators from mast cells in the airway.

Albuterol has been shown in most clinical trials to have more effect on the respiratory tract, in the form of bronchial smooth muscle relaxation, than isoproterenol at comparable doses while producing fewer cardiovascular effects. Controlled clinical studies and other clinical experience have shown that inhaled albuterol, like other beta-adrenergic agonist drugs, can produce a significant cardiovascular effect in some patients, as measured by pulse rate, blood pressure, symptoms, and/or electrocardiographic changes.

Preclinical Intravenous studies in rats with albuterol sulfate have demonstrated that albuterol crosses the blood-brain barrier and reaches brain concentrations amounting to approximately 5% of the plasma concentrations. In structures outside the blood-brain barrier (pineal and pituitary glands), albuterol concentrations were found to be 100 times those in the whole brain.

Studies in laboratory animals (minipigs, rodents, and dogs) have demonstrated the occurrence of cardiac arrhythmias and sudden death (with histologic evidence of myocardial necrosis) when beta 2-agonist and methylxanthines were administered concurrently. The clinical significance of these findings is unknown.

Propellant HFA-134a is devoid of pharmacological activity except at very high doses in animals (380-1300 times the maximum human exposure based on comparisons of AUC values), primarily producing ataxia, tremors, dyspnea, or salivation. These are similar to effects produced by the structurally related chlorofluorocarbons (CFCs), which have been used extensively in metered dose inhalers.

In animals and humans, propellant HFA-134a was found to be rapidly absorbed and rapidly eliminated, with an elimination half-life of 3 to 27 minutes in animals and 5 to 7 minutes in humans. Time to maximum plasma concentration (Tmax) and mean residence time are both extremely short, leading to a transient appearance of HFA-134a in the blood with no evidence of accumulation.

PHARMACOKINETICS

Pharmacokinetics In a single-dose bioavailability study which enrolled six healthy, male volunteers, transient low albuterol levels (close to the lower limit of quantitation) were observed after administration of two puffs from both Albuterol Sulfate Inhalation Aerosol and a CFC 11/12 propelled albuterol inhaler. No formal pharmacokinetic analyses were possible for either treatment, but systemic albuterol levels appeared similar.

Clinical Trials In a 12-week, randomized, double-blind, double-dummy, active- and placebo-controlled trial, 565 patients with asthma were evaluated for the bronchodilator efficacy of Albuterol Sulfate Inhalation Aerosol (193 patients) in comparison to a CFC 11/12 propelled albuterol inhaler (186 patients) and an HFA-134a placebo inhaler (186 patients).

Serial FEV 1 measurements (shown below as percent change from test-day baseline) demonstrated that two inhalations of Albuterol Sulfate Inhalation Aerosol produced significantly greater improvement in pulmonary function than placebo and produced outcomes which were clinically comparable to a CFC 11/12 propelled albuterol inhaler.

The mean time to onset of a 15% increase in FEV 1 was 6 minutes and the mean time to peak effect was 50 to 55 minutes. The mean duration of effect as measured by a 15% increase in FEV 1 was 3 hours. In some patients, duration of effect was as long as 6 hours.

In another clinical study in adults, two inhalations of Albuterol Sulfate Inhalation Aerosol taken 30 minutes before exercise prevented exercise-induced bronchospasm as demonstrated by the maintenance of FEV 1 within 80% of baseline values in the majority of patients.

In a 4-week, randomized, open-label trial, 63 children, 4 to 11 years of age, with asthma were evaluated for the bronchodilator efficacy of Albuterol Sulfate Inhalation Aerosol (33 pediatric patients) in comparison to a CFC 11/12 propelled albuterol inhaler (30 pediatric patients).

Serial FEV 1 measurements as percent change from test-day baseline demonstrated that two inhalations of Albuterol Sulfate Inhalation Aerosol produced outcomes which were clinically comparable to a CFC 11/12 propelled albuterol inhaler.

The mean time to onset of a 12% increase in FEV 1 for Albuterol Sulfate Inhalation Aerosol was 7 minutes and the mean time to peak effect was approximately 50 minutes. The mean duration of effect as measured by a 12% increase in FEV 1 was 2.3 hours. In some pediatric patients, duration of effect was as long as 6 hours.

In another clinical study in pediatric patients, two inhalations of Albuterol Sulfate Inhalation Aerosol taken 30 minutes before exercise provided comparable protection against exercise-induced bronchospasm as a CFC 11/12 propelled albuterol inhaler.

INDICATIONS AND USAGE

Albuterol Sulfate Inhalation Aerosol is indicated in adults and children 4 years of age and older for the treatment or prevention of bronchospasm with reversible obstructive airway disease and for the prevention of exercise-induced bronchospasm.

CONTRAINDICATIONS

Albuterol Sulfate Inhalation Aerosol is contraindicated in patients with a history of hypersensitivity to albuterol or any other Albuterol Sulfate Inhalation Aerosol components.

WARNINGS

1. Paradoxical Bronchospasm: Inhaled albuterol sulfate can produce paradoxical bronchospasm that may be life threatening. If paradoxical bronchospasm occurs, Albuterol Sulfate Inhalation Aerosol should be discontinued immediately and alternative therapy instituted. It should be recognized that paradoxical bronchospasm, when associated with inhaled formulations, frequently occurs with the first use of a new canister.
2. Deterioration of Asthma: Asthma may deteriorate acutely over a period of hours or chronically over several days or longer. If the patient needs more doses of Albuterol Sulfate Inhalation Aerosol than usual, this may be a marker of destabilization of asthma and requires re-evaluation of the patient and treatment regimen, giving special consideration to the possible need for anti-inflammatory treatment, e.g., corticosteroids.
3. Use of Anti-inflammatory Agents: The use of beta-adrenergic-agonist bronchodilators alone may not be adequate to control asthma in many patients. Early consideration should be given to adding anti-inflammatory agents, e.g., corticosteroids, to the therapeutic regimen.
Cardiovascular Effects: Albuterol Sulfate Inhalation Aerosol, like other beta-adrenergic agonists, can produce clinically significant cardiovascular effects in some patients as measured by pulse rate, blood pressure, and/or symptoms. Although such effects are uncommon after administration of Albuterol Sulfate Inhalation Aerosol at recommended doses, if they occur, the drug may need to be discontinued. In addition, beta-agonists have been reported to produce ECG changes, such as flattening of the T wave, prolongation of the QTc interval, and ST segment depression. The clinical significance of these findings is unknown. Therefore, Albuterol Sulfate Inhalation Aerosol, like all sympathomimetic amines, should be used with caution in patients with cardiovascular disorders, especially coronary insufficiency, cardiac arrhythmias, and hypertension.
4. Do Not Exceed Recommended Dose: Fatalities have been reported in association with excessive use of inhaled sympathomimetic drugs in patients with asthma. The exact cause of death is unknown, but cardiac arrest following an unexpected development of a severe acute asthmatic crisis and subsequent hypoxia is suspected.
5. Immediate Hypersensitivity Reactions: Immediate hypersensitivity reactions may occur after administration of albuterol sulfate, as demonstrated by rare cases of urticaria, angioedema, rash, bronchospasm, anaphylaxis, and oropharyngeal edema.

PRECAUTIONS

GENERAL PRECAUTIONS

General Albuterol sulfate, as with all sympathomimetic amines, should be used with caution in patients with cardiovascular disorders, especially coronary insufficiency, cardiac arrhythmias, and hypertension; in patients with convulsive disorders, hyperthyroidism, or diabetes mellitus; and in patients who are unusually responsive to sympathomimetic amines. Clinically significant changes in systolic and diastolic blood pressure have been seen in individual patients and could be expected to occur in some patients after use of any beta-adrenergic bronchodilator.

Large doses of intravenous albuterol have been reported to aggravate preexisting diabetes mellitus and ketoacidosis. As with other beta-agonists, albuterol may produce significant hypokalemia in some patients, possibly through intracellular shunting, which has the potential to produce adverse cardiovascular effects. The decrease is usually transient, not requiring supplementation.

PATIENT COUNSELING INFORMATION

Information for Patients See illustrated Patient's Instructions for Use. SHAKE WELL BEFORE USING. Patients should be given the following information:

It is recommended to prime the inhaler before using for the first time and in cases where the inhaler has not been used for more than 2 weeks by releasing four “test sprays” into the air, away from the face.

KEEPING THE PLASTIC MOUTHPIECE CLEAN IS VERY IMPORTANT TO PREVENT MEDICATION BUILDUP AND BLOCKAGE. THE MOUTHPIECE SHOULD BE WASHED, SHAKEN TO REMOVE EXCESS WATER, AND AIR DRIED THOROUGHLY AT LEAST ONCE A WEEK. INHALER MAY CEASE TO DELIVER MEDICATION IF NOT PROPERLY CLEANED.

The mouthpiece should be cleaned (with the canister removed) by running warm water through the top and bottom for 30 seconds at least once a week. The mouthpiece must be shaken to remove excess water, then air dried thoroughly (such as overnight). Blockage from medication buildup or improper medication delivery may result from failure to thoroughly air dry the mouthpiece.

If the mouthpiece should become blocked (little or no medication coming out of the mouthpiece), the blockage may be removed by washing as described above.

If it is necessary to use the inhaler before it is completely dry, shake off excess water, replace canister, test spray twice away from face, and take the prescribed dose. After such use, the mouthpiece should be rewashed and allowed to air dry thoroughly.

The action of Albuterol Sulfate Inhalation Aerosol should last up to 4 to 6 hours. Albuterol Sulfate Inhalation Aerosol should not be used more frequently than recommended. Do not increase the dose or frequency of doses of Albuterol Sulfate Inhalation Aerosol without consulting your physician. If you find that treatment with Albuterol Sulfate Inhalation Aerosol becomes less effective for symptomatic relief, your symptoms become worse, and/or you need to use the product more frequently than usual, medical attention should be sought immediately. While you are taking Albuterol Sulfate Inhalation Aerosol, other inhaled drugs and asthma medications should be taken only as directed by your physician.

Common adverse effects of treatment with inhaled albuterol include palpitations, chest pain, rapid heart rate, tremor, or nervousness. If you are pregnant or nursing, contact your physician about use of Albuterol Sulfate Inhalation Aerosol. Effective and safe use of Albuterol Sulfate Inhalation Aerosol includes an understanding of the way that it should be administered. Use Albuterol Sulfate Inhalation Aerosol only with the actuator supplied with the product. Discard the canister after 200 sprays have been used.

In general, the technique for administering Albuterol Sulfate Inhalation Aerosol to children is similar to that for adults. Children should use Albuterol Sulfate Inhalation Aerosol under adult supervision, as instructed by the patient's physician. (See Patient's Instructions for Use.)

Drug Interactions

1. Beta-Blockers: Beta-adrenergic-receptor blocking agents not only block the pulmonary effect of beta-agonists, such as Albuterol Sulfate Inhalation Aerosol, but may produce severe bronchospasm in asthmatic patients. Therefore, patients with asthma should not normally be treated with beta-blockers. However, under certain circumstances, e.g., as prophylaxis after myocardial infarction, there may be no acceptable alternatives to the use of beta-adrenergic blocking agents in patients with asthma. In this setting, cardioselective beta-blockers should be considered, although they should be administered with caution.
2. Diuretics: The ECG changes and/or hypokalemia which may result from the administration of nonpotassium-sparing diuretics (such as loop or thiazide diuretics) can be acutely worsened by beta-agonists, especially when the recommended dose of the beta-agonist is exceeded. Although the clinical significance of these effects is not known, caution is advised in the coadministration of beta-agonists with nonpotassium-sparing diuretics.
3. Albuterol-Digoxin: Mean decreases of 16% and 22% in serum digoxin levels were demonstrated after single-dose intravenous and oral administration of albuterol, respectively, to normal volunteers who had received digoxin for 10 days. The clinical significance of these findings for patients with obstructive airway disease who are receiving albuterol and digoxin on a chronic basis is unclear; nevertheless, it would be prudent to carefully evaluate the serum digoxin levels in patients who are currently receiving digoxin and albuterol.
4. Monoamine Oxidase Inhibitors or Tricyclic Antidepressants: Albuterol Sulfate Inhalation Aerosol should be administered with extreme caution to patients being treated with monoamine oxidase inhibitors or tricyclic antidepressants, or within 2 weeks of discontinuation of such agents, because the action of albuterol on the cardiovascular system may be potentiated.

Carcinogenesis, Mutagenesis, and Impairment of Fertility

In a 2-year study in SPRAGUE-DAWLEY ® rats, albuterol sulfate caused a dose-related increase in the incidence of benign leiomyomas of the mesovarium at the above dietary doses of 2 mg/kg (approximately 15 times the maximum recommended daily inhalation dose for adults on a mg/m ^2 basis and approximately 6 times the maximum recommended daily inhalation dose for children on a mg/m ^2 basis). In another study this effect was blocked by the coadministration of propranolol, a nonselective beta-adrenergic antagonist. In an 18-month study in CD-1 mice, albuterol sulfate showed no evidence of tumorigenicity at dietary doses of up to 500 mg/kg (approximately 1700 times the maximum recommended daily inhalation dose for adults on a mg/m ^2 basis and approximately 800 times the maximum recommended daily inhalation dose for children on a mg/m ^2 basis). In a 22-month study in Golden Hamsters, albuterol sulfate showed no evidence of tumorigenicity at dietary doses of up to 50 mg/kg (approximately 225 times the maximum recommended daily inhalation dose for adults on a mg/m ^2 basis and approximately 110 times the maximum recommended daily inhalation dose for children on a mg/m ^2 basis).

Albuterol sulfate was not mutagenic in the Ames test or a mutation test in yeast. Albuterol sulfate was not clastogenic in a human peripheral lymphocyte assay or in an AH1 strain mouse micronucleus assay.

Reproduction studies in rats demonstrated no evidence of impaired fertility at oral doses up to 50 mg/kg (approximately 340 times the maximum recommended daily inhalation dose for adults on a mg/m ^2 basis).

Pregnancy Teratogenic Effects Pregnancy

Albuterol sulfate has been shown to be teratogenic in mice. A study in CD-1 mice given albuterol sulfate subcutaneously showed cleft palate formation in 5 of 111 (4.5%) fetuses at 0.25 mg/kg (less than the maximum recommended daily inhalation dose for adults on a mg/m ^2 basis) and in 10 of 108 (9.3%) fetuses at 2.5 mg/kg (approximately 8 times the maximum recommended daily inhalation dose for adults on a mg/m ^2 basis). The drug did not induce cleft palate formation at a dose of 0.025 mg/kg (less than the maximum recommended daily inhalation dose for adults on a mg/m ^2 basis). Cleft palate also occurred in 22 of 72 (30.5%) fetuses from females treated subcutaneously with 2.5 mg/kg of isoproterenol (positive control).

A reproduction study in Stride Dutch rabbits revealed cranioschisis in 7 of 19 (37%) fetuses when albuterol sulfate was administered orally at 50 mg/kg dose (approximately 680 times the maximum recommended daily inhalation dose for adults on a mg/m ^2 basis).

In an inhalation reproduction study in SPRAGUE-DAWLEY rats, the albuterol sulfate/HFA-134a formulation did not exhibit any teratogenic effects at 10.5 mg/kg (approximately 70 times the maximum recommended daily inhalation dose for adults on a mg/m ^2 basis).

A study in which pregnant rats were dosed with radiolabeled albuterol sulfate demonstrated that drug-related material is transferred from the maternal circulation to the fetus.

There are no adequate and well-controlled studies of Albuterol Sulfate Inhalation Aerosol or albuterol sulfate in pregnant women. Albuterol Sulfate Inhalation Aerosol should be used during pregnancy only if the potential benefit justifies the potential risk to the fetus.

During worldwide marketing experience, various congenital anomalies, including cleft palate and limb defects, have been reported in the offspring of patients being treated with albuterol. Some of the mothers were taking multiple medications during their pregnancies. Because no consistent pattern of defects can be discerned, a relationship between albuterol use and congenital anomalies has not been established.

Use in Labor and Delivery

Because of the potential for beta-agonist interference with uterine contractility, use of Albuterol Sulfate Inhalation Aerosol for relief of bronchospasm during labor should be restricted to those patients in whom the benefits clearly outweigh the risk.

Tocolysis: Albuterol has not been approved for the management of preterm labor. The benefit:risk ratio when albuterol is administered for tocolysis has not been established. Serious adverse reactions, including pulmonary edema, have been reported during or following treatment of premature labor with beta 2-agonists, including albuterol.

Nursing Mothers

Plasma levels of albuterol sulfate and HFA-134a after inhaled therapeutic doses are very low in humans, but it is not known whether the components of Albuterol Sulfate Inhalation Aerosol are excreted in human milk.

Because of the potential for tumorigenicity shown for albuterol in animal studies and lack of experience with the use of Albuterol Sulfate Inhalation Aerosol by nursing mothers, a decision should be made whether to discontinue nursing or to discontinue the drug, taking into account the importance of the drug to the mother. Caution should be exercised when albuterol sulfate is administered to a nursing woman.

Pediatrics

The safety and effectiveness of Albuterol Sulfate Inhalation Aerosol in pediatric patients below the age of 4 years have not been established.

Geriatrics

Albuterol Sulfate Inhalation Aerosol has not been studied in a geriatric population. As with other beta 2-agonists, special caution should be observed when using Albuterol Sulfate Inhalation Aerosol in elderly patients who have concomitant cardiovascular disease that could be adversely affected by this class of drug.

ADVERSE REACTIONS

Adverse reaction information concerning Albuterol Sulfate Inhalation Aerosol is derived from a 12-week, double-blind, double-dummy study which compared Albuterol Sulfate Inhalation Aerosol, a CFC 11/12 propelled albuterol inhaler, and an HFA-134a placebo inhaler in 565 asthmatic patients. The following table lists the incidence of all adverse events (whether considered by the investigator drug related or unrelated to drug) from this study which occurred at a rate of 3% or greater in the Albuterol Sulfate Inhalation Aerosol treatment group and more frequently in the Albuterol Sulfate Inhalation Aerosol treatment group than in the placebo group. Overall, the incidence and nature of the adverse reactions reported for Albuterol Sulfate Inhalation Aerosol and a CFC 11/12 propelled albuterol inhaler were comparable.

Adverse Experience Incidences (% of patients) in a Large 12-week Clinical Trial*
Body System/ Adverse Event (Preferred Term) |  | Albuterol Sulfate Inhalation Aerosol (N=193) | CFC 11/12 Propelled Albuterol Inhaler (N=186) | HFA-134a Placebo Inhaler (N=186)
Application Site Disorders | Inhalation Site Sensation | 6 | 9 | 2
Application Site Disorders | Inhalation Taste Sensation | 4 | 3 | 3
Body as a Whole | Allergic Reaction/Symptoms | 6 | 4 | <1
Body as a Whole | Back Pain | 4 | 2 | 3
Body as a Whole | Fever | 6 | 2 | 5
Central and Peripheral Nervous System | Tremor | 7 | 8 | 2
Gastrointestinal System | Nausea | 10 | 9 | 5
Gastrointestinal System | Vomiting | 7 | 2 | 3
Heart Rate and Rhythm Disorder | Tachycardia | 7 | 2 | <1
Psychiatric Disorders | Nervousness | 7 | 9 | 3
Respiratory System Disorders | Respiratory Disorder (unspecified) | 6 | 4 | 5
Respiratory System Disorders | Rhinitis | 16 | 22 | 14
Respiratory System Disorders | Upper Resp Tract Infection | 21 | 20 | 18
Urinary System Disorder | Urinary Tract Infection | 3 | 4 | 2
*This table includes all adverse events (whether considered by the investigator drug related or unrelated to drug) which occurred at an incidence rate of at least 3% in the Albuterol Sulfate Inhalation Aerosol group and more frequently in the Albuterol Sulfate Inhalation Aerosol group than in the HFA-134a placebo inhaler group.

Adverse events reported by less than 3% of the patients receiving Albuterol Sulfate Inhalation Aerosol, and by a greater proportion of Albuterol Sulfate Inhalation Aerosol patients than placebo patients, which have the potential to be related to Albuterol Sulfate Inhalation Aerosol include: dysphonia, increased sweating, dry mouth, chest pain, edema, rigors, ataxia, leg cramps, hyperkinesia, eructation, flatulence, tinnitus, diabetes mellitus, anxiety, depression, somnolence, rash. Palpitation and dizziness have also been observed with Albuterol Sulfate Inhalation Aerosol.

Adverse events reported in a 4-week pediatric clinical trial comparing Albuterol Sulfate Inhalation Aerosol and a CFC 11/12 propelled albuterol inhaler occurred at a low incidence rate and were similar to those seen in the adult trials.

In small, cumulative dose studies, tremor, nervousness, and headache appeared to be dose related.

Rare cases of urticaria, angioedema, rash, bronchospasm, and oropharyngeal edema have been reported after the use of inhaled albuterol. In addition, albuterol, like other sympathomimetic agents, can cause adverse reactions such as hypertension, angina, vertigo, central nervous system stimulation, insomnia, headache, metabolic acidosis, and drying or irritation of the oropharynx.

To report SUSPECTED ADVERSE REACTIONS, contact Sandoz Inc., at 1-800-525-8747 or FDA at 1-800-FDA-1088 or www.fda.gov/medwatch.

OVERDOSAGE

The expected symptoms with overdosage are those of excessive beta-adrenergic stimulation and/or occurrence or exaggeration of any of the symptoms listed under ADVERSE REACTIONS, e.g., seizures, angina, hypertension or hypotension, tachycardia with rates up to 200 beats per minute, arrhythmias, nervousness, headache, tremor, dry mouth, palpitation, nausea, dizziness, fatigue, malaise, and insomnia.

Hypokalemia may also occur. As with all sympathomimetic medications, cardiac arrest and even death may be associated with abuse of Albuterol Sulfate Inhalation Aerosol. Treatment consists of discontinuation of Albuterol Sulfate Inhalation Aerosol together with appropriate symptomatic therapy. The judicious use of a cardioselective beta-receptor blocker may be considered, bearing in mind that such medication can produce bronchospasm. There is insufficient evidence to determine if dialysis is beneficial for overdosage of Albuterol Sulfate Inhalation Aerosol.

The oral median lethal dose of albuterol sulfate in mice is greater than 2000 mg/kg (approximately 6800 times the maximum recommended daily inhalation dose for adults on a mg/m ^2 basis and approximately 3200 times the maximum recommended daily inhalation dose for children on a mg/m ^2 basis). In mature rats, the subcutaneous median lethal dose of albuterol sulfate is approximately 450 mg/kg (approximately 3000 times the maximum recommended daily inhalation dose for adults on a mg/m ^2 basis and approximately 1400 times the maximum recommended daily inhalation dose for children on a mg/m ^2 basis). In young rats, the subcutaneous median lethal dose is approximately 2000 mg/kg (approximately 14,000 times the maximum recommended daily inhalation dose for adults on a mg/m ^2 basis and approximately 6400 times the maximum recommended daily inhalation dose for children on a mg/m ^2 basis). The inhalation median lethal dose has not been determined in animals.

DOSAGE AND ADMINISTRATION

For treatment of acute episodes of bronchospasm or prevention of asthmatic symptoms, the usual dosage for adults and children 4 years of age and older is two inhalations repeated every 4 to 6 hours. More frequent administration or a larger number of inhalations is not recommended. In some patients, one inhalation every 4 hours may be sufficient. Each actuation of Albuterol Sulfate Inhalation Aerosol delivers 108 mcg of albuterol sulfate (equivalent to 90 mcg of albuterol base) from the mouthpiece. It is recommended to prime the inhaler before using for the first time and in cases where the inhaler has not been used for more than 2 weeks by releasing four “test sprays” into the air, away from the face.

Exercise Induced Bronchospasm Prevention: The usual dosage for adults and children 4 years of age and older is two inhalations 15 to 30 minutes before exercise.

To maintain proper use of this product, it is important that the mouthpiece be washed and dried thoroughly at least once a week. The inhaler may cease to deliver medication if not properly cleaned and dried thoroughly (see PRECAUTIONS, Information for Patients section). Keeping the plastic mouthpiece clean is very important to prevent medication buildup and blockage. The inhaler may cease to deliver medication if not properly cleaned and air dried thoroughly. If the mouthpiece becomes blocked, washing the mouthpiece will remove the blockage.

If a previously effective dose regimen fails to provide the usual response, this may be a marker of destabilization of asthma and requires reevaluation of the patient and the treatment regimen, giving special consideration to the possible need for anti-inflammatory treatment, e.g., corticosteroids.

HOW SUPPLIED

Albuterol Sulfate Inhalation Aerosol is supplied as a pressurized aluminum canister, with an attached dose indicator, a yellow plastic actuator and orange dust cap each in boxes of one. Each actuation delivers 120 mcg of albuterol sulfate from the valve and 108 mcg of albuterol sulfate from the mouthpiece (equivalent to 90 mcg of albuterol base). Canisters with a labeled net weight of 6.7 g contain 200 inhalations (NDC 68788-7996-2).

Rx only. Store between 15° to 25°C (59° to 77°F). Store the inhaler with the mouthpiece down. For best results, canister should be at room temperature before use.

SHAKE WELL BEFORE USING.

The yellow actuator supplied with Albuterol Sulfate Inhalation Aerosol should not be used with any other product canisters, and actuator from other products should not be used with a Albuterol Sulfate Inhalation Aerosol canister. The correct amount of medication in each canister cannot be assured after 200 actuations and when the dose indicator display window shows zero, even though the canister is not completely empty the canister is not completely empty. The canister should be discarded when the labeled number of actuations have been used.

WARNING: Avoid spraying in eyes. Contents under pressure. Do not puncture or incinerate. Exposure to temperatures above 120°F may cause bursting. Keep out of reach of children.

Albuterol Sulfate Inhalation Aerosol does not contain chlorofluorocarbons (CFCs) as the propellant.

Developed and Manufactured by:

Kindeva Drug Delivery L.P.

Northridge, CA 91324, USA

or

Kindeva Drug Delivery Limited

Loughborough, UK

Relabeled By: Preferred Pharmaceuticals Inc.

Distributed by:
Sandoz Inc.
Princeton, NJ 08540

Copyright © 1996, 2011, 2012, 2017, 2018, 2020, 2025
All rights reserved.

The trademarks depicted in this piece are owned by their respective companies.

Revised: 03/2025 3200001123

INSTRUCTIONS FOR USE
Albuterol Sulfate (al-BYOO-ter-ole)
Inhalation Aerosol with Dose Indicator

Read this Instructions for Use before you start using Albuterol Sulfate Inhalation Aerosol and eachtime you get a refill. There may be new information. This information does not take the place of talking to your doctor about your medical condition or treatment. Your doctor should show you how your child should use Albuterol Sulfate Inhalation Aerosol.

Important Information:

- Albuterol Sulfate Inhalation Aerosol is for oral inhalation use only.
- Take Albuterol Sulfate Inhalation Aerosol exactly as your doctor tells you to.

Albuterol Sulfate Inhalation Aerosol comes as a canister with a dose indicator. The dose indicator is located on the top of the canister that fits into an actuator (See). The dose indicator display window will show you how many puffs of medicine you have left. A puff of medicine is released each time you press the center of the dose indicator.

- Do not use the Albuterol Sulfate Inhalation Aerosol actuator with a canister of medicine from any other inhaler.
- Do not use the Albuterol Sulfate Inhalation Aerosol canister with an actuator from any other inhaler.

Figure A

Before you use Albuterol Sulfate Inhalation Aerosol for the first time make sure that the pointer on the dose indicator is pointing to the right of the “200” inhalation mark in the dose indicator display window (See) .

Each canister of Albuterol Sulfate Inhalation Aerosol contains 200 puffs of medicine. This does not include the sprays of medicine used for priming your inhaler.

- The dose indicator display window will continue to move after every 10 puffs.
- The number in the dose indicator display window will continue to change after every 20 puffs.
- The color in the dose indicator display window will change to red, as shown in the shaded area, when there are only 20 puffs of medicine left in your inhaler (See) . This is when you need to refill your prescription or ask your doctor if you need another prescription for Albuterol Sulfate Inhalation Aerosol.

Figure B

Before using your Albuterol Sulfate Inhalation Aerosol for the first time, you should prime your inhaler. If you do not use your Albuterol Sulfate Inhalation Aerosol for more than 2 weeks, you should re-prime it before use.

- Remove the cap from the mouthpiece (See). Check inside the mouthpiece for objects before use.
- Make sure the canister is fully inserted into the actuator.
- Hold the inhaler in an upright position away from your face and shake the inhaler well.
- Press down fully on the center of the dose indicator to release a spray of medicine. You may hear a soft click from the dose indicator as it counts down during use.
- Repeat the priming step 3 more times to release a total of 4 sprays of medicine. Shake the inhaler well before each priming spray.
- After the 4 priming sprays, the dose indicator should be pointing to 200. There are now 200 puffs of medicine left in the canister.
- Your inhaler is now ready to use.

Using your Albuterol Sulfate Inhalation Aerosol inhaler:

Step 1: Shake the inhaler well before each use. Remove the cap from the mouthpiece (See). Check inside the mouthpiece for objects before use. Make sure the canister is fully inserted into the actuator.

Figure C

Step 2: Breathe out as fully as you comfortably can through your mouth. Hold the inhaler in the upright position with the mouthpiece pointing towards you and place the mouthpiece fully into the mouth (See). Close your lips around the mouthpiece.

Figure D

Step 3: While breathing in deeply and slowly, press down on the center of the dose indicator with your index finger until the canister stops moving in the actuator and a puff of medicine has been released (See). Then stop pressing the dose indicator.

Step 4: Hold your breath as long as you comfortably can, up to 10 seconds. Remove the inhaler from your mouth, and then breathe out.

Step 5: If your doctor has prescribed additional puffs of Albuterol Sulfate Inhalation Aerosol, wait 1 minute then shake the inhaler well. Repeat steps 3 through 5 in the section “ ”.

Step 6: Replace the cap right away after use.

Cleaning your Albuterol Sulfate Inhalation Aerosol inhaler:

It is very important that you keep the mouthpiece clean so that medicine will not build up and block the spray through the mouthpiece. Clean the mouthpiece 1 time each week or if your mouthpiece becomes blocked (See).

Step 1: Remove the canister from the actuator and take the cap off the mouthpiece. Do not clean the metal canister or let it get wet.

Step 2: Wash the mouthpiece through the top and bottom with warm running water for 30 seconds (See).

Figure E

Step 3: Shake off as much water from the mouthpiece as you can.

Step 4: Look in the mouthpiece to make sure any medicine buildup has been completely washed away. If the mouthpiece is blocked with buildup, little to no medicine will come out of the mouthpiece (See). If there is any buildup, repeat Steps 2 through 4 in the section “ ”.

Figure F

Step 5: Let the mouthpiece air-dry such as overnight (Figure G). Do not put the canister back into the actuator if it is still we

Figure G

Step 6: When the mouthpiece is dry, put the canister back in the actuator and put the cap on the mouthpiece.

Note: If you need to use your Albuterol Sulfate Inhalation Aerosol inhaler before it is completely dry, put the canister back in the actuator and shake the inhaler well. Press down on the center of the dose indicator 2 times to release a total of 2 sprays into the air, away from your face. Take your dose as prescribed then clean and air-dry your inhaler as described in the section “ ”.

How should I store Albuterol Sulfate Inhalation Aerosol?

- Store Albuterol Sulfate Inhalation Aerosol at room temperature between 59°F and 77°F (15°C and 25°C).
- Store with the mouthpiece down.
- Avoid exposing Albuterol Sulfate Inhalation Aerosol to extreme heat and cold.
- Do not puncture or burn the canister.
- Keep your Albuterol Sulfate Inhalation Aerosol inhaler and all medicines out of the reach of children.

Developed and Manufactured by:
Kindeva Drug Delivery L.P.
Northridge, CA 91324, USA

or

Kindeva Drug Delivery Limited

Loughborough, UK

Distributed by:
Sandoz Inc.
Princeton, NJ 08540

Copyright © 1996, 2011, 2012, 2017, 2018, 2020, 2025

All rights reserved.

This Instructions for Use has been approved by the U.S. Food and Drug Administration.

Revised: 03/2025 3200001123

Relabeled By: Preferred Pharmaceuticals Inc.

PACKAGE LABEL

Principal Display Panel – Canister

NDC 0781- 7296-85

Albuterol Sulfate
Inhalation Aerosol HFA

90 mcg *

with Dose Indicator

Rx only

FOR ORAL INHALATION WITH
SANDOZ INC. ALBUTEROL SULFATE

INHALATION AEROSOL HFA

ACTUATOR ONLY

200 METERED INHALATIONS
Net Contents 6.7 g

SANDOZ

Relabeled By: Preferred Pharmaceuticals Inc.